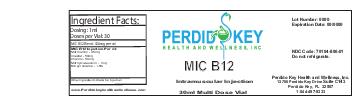 DRUG LABEL: MIC B12
NDC: 70104-806 | Form: INJECTION
Manufacturer: Perdido Key Health and Wellness Inc
Category: prescription | Type: HUMAN PRESCRIPTION DRUG LABEL
Date: 20151123

ACTIVE INGREDIENTS: INOSITOL 1 mg/1 mL; CHOLINE C-11 1 mg/1 mL; METHYLCOBALAMIN 1 mg/1 mL; L-METHIONINE-S,R-SULFOXIMINE 1 mg/1 mL

DOSAGE FORMS AND STRENGTHS

1ml